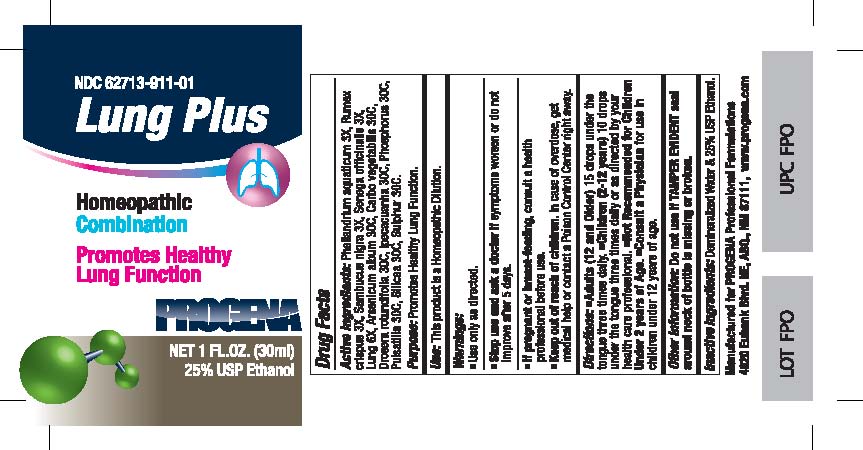 DRUG LABEL: Progena
NDC: 62713-911 | Form: LIQUID
Manufacturer: Meditrend, Inc. DBA Progena Professional Formulations
Category: homeopathic | Type: HUMAN OTC DRUG LABEL
Date: 20151201

ACTIVE INGREDIENTS: OENANTHE AQUATICA FRUIT 3 [hp_X]/1 mL; RUMEX CRISPUS ROOT 3 [hp_X]/1 mL; SAMBUCUS NIGRA FLOWERING TOP 3 [hp_X]/1 mL; POLYGALA SENEGA ROOT 3 [hp_X]/1 mL; SUS SCROFA LUNG 6 [hp_X]/1 mL; ARSENIC TRIOXIDE 30 [hp_C]/1 mL; ACTIVATED CHARCOAL 30 [hp_C]/1 mL; DROSERA ROTUNDIFOLIA 30 [hp_C]/1 mL; IPECAC 30 [hp_C]/1 mL; PHOSPHORUS 30 [hp_C]/1 mL; PULSATILLA VULGARIS 30 [hp_C]/1 mL; SILICON DIOXIDE 30 [hp_C]/1 mL; SULFUR 30 [hp_C]/1 mL
INACTIVE INGREDIENTS: WATER; ALCOHOL

Lung Plus

ACTIVE INGREDIENT

Active Ingredients:Phellandrium aquaticum 3X, Rumex crispus 3X, Sambucus nigra 3X, Senega officinalis 3X, Lung 6X, Arsenicum album 30C, Carbo vegetabilis 30C, Drosera rotundifolia 30C, Ipecacuanha 30C, Phosphorus 30C, Pulsatilla 30C, Silicea 30C, Sulphur 30C.

Purpose:Promotes Healthy Lung Function.

INDICATIONS AND USAGE

Use:This product is a Homeopathic Dilution.

Keep Out of Reach of Children. In case of overdose, get medical help or contact a
Poison Control Center right away.

Warnings:

- Use Only as directed.
- Stop use and ask a doctor ifsymptoms worsen or do not improve after 5 days.
- If pregnant or breast-feeding, consult a health professional before use.

DOSAGE AND ADMINISTRATION

Directions:• Adults (12 and Older)15 drops under the tongue three times daily.• Children (2-12 years)10 drops under the tongue three times daily or as directed by your health care professional.• Not Recommended for Children Under 2 years of Age.• Consult a Physicianfor use in children under 12 years of age.

Other Information: Do not use if TAMPER EVIDENT seal around neck of bottle is missing or broken.

Inactive Ingredients:Demineralized Water and 25% USP Ethanol.

PACKAGE LABEL

Manufactured for Progena Professional Formulations
4820 Eubank Blvd. NE, ABQ, NM 87111, www.progena.com